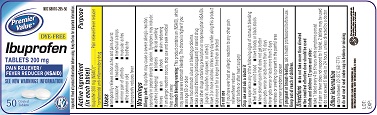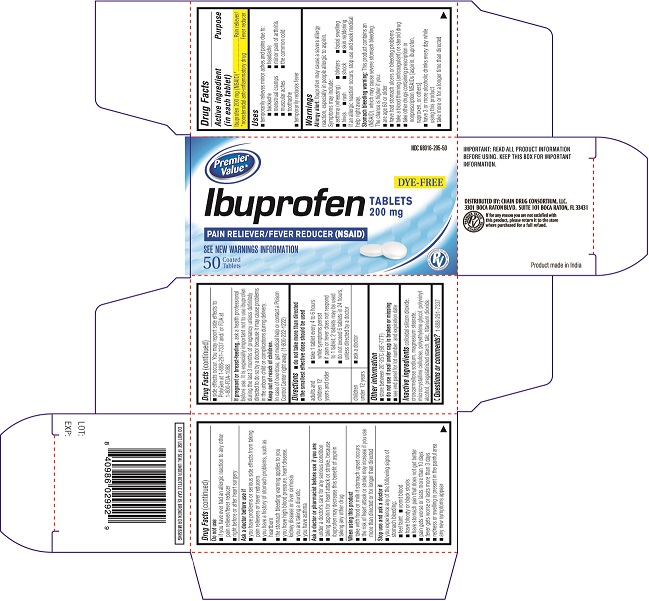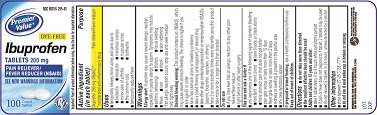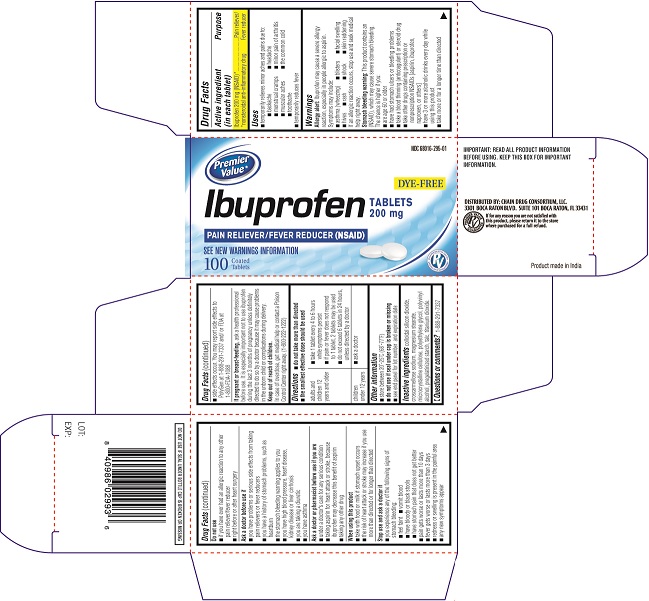 DRUG LABEL: Ibuprofen
NDC: 68016-295 | Form: TABLET, FILM COATED
Manufacturer: Chain Drug Consortium LLC
Category: otc | Type: Human OTC Drug Label
Date: 20130429

ACTIVE INGREDIENTS: IBUPROFEN 200 mg/1 1
INACTIVE INGREDIENTS: CELLULOSE, MICROCRYSTALLINE; CROSCARMELLOSE SODIUM; STARCH, CORN; TALC; COLLOIDAL SILICON DIOXIDE; MAGNESIUM STEARATE

ACTIVE INGREDIENT(S)

Ibuprofen 200 mg (NSAID)*

· nonsteroidal anti-inflammatory drug

PURPOSE

Pain reliever / fever reducer

USE(S)

- temporarily relieves minor aches and pain due to :
- backache
- headache
- menstrual cramps
- minor pain of arthritis
- muscular aches
- the common cold
- toothache
- Temporarily reduces fever

WARNINGS

Allergy alerts: Ibuprofen may cause a severe allergy reaction, especially in people allergic to aspirin.

Symptoms may include:

- asthma (wheezing)
- blisters
- facial swelling
- hives
- rash
- shock
- skin reddening

If an allergic reaction occurs, stop use and seek medical help right away.

Stomach bleeding warning: This product contains a nonsteroidal anti-inflammatory drug (NSAID), which may cause stomach bleeding. The chance is higher if you:

- are age 60 or older
- have bad stomach ulcers or bleeding problems
- take a blood thinning (anticoagulant) or steroid drug
- take other drug containing prescription NSAID (aspirin, ibuprofen, naproxen, or others)
- have 3 or more alcoholic drinks every day while using this product
- the more or for a longer time than directed

DO NOT USE

- if you have ever had an allergic reaction to any other pain reliever/fever reducer
- right before or after heart surgery

ASK A DOCTOR BEFORE USE IF

you have

- problems or serious side effects from taking pain relievers or fever reducers
- stomach problems that last or come back, such as heartburn, upset stomach, or stomach pain
- ulcers
- bleeding problems
- high blood pressure
- heart or kidney disease
- taken a diuretics
- reached age 60 or older

ASK A DOCTOR OR PHARMACIST BEFORE USE IF

you are

- taking any other drugs containg an NSAID (prescription or nonprescription)
- taking a blood thining (anticoagulant) or steriod drug
- under a doctor’s care for any serious condition
- taking aspirin for heart attacks or stroke, because ibuprofen may decrease this benefit of aspirin
- taking any other drug

WHEN USING THIS PRODUCT

- take with food or milk if stomach upset occurs
- long term continuous use may increase the risk of heart attack or stroke

STOP USE AND ASK DOCTOR IF

- you feel faint, vomit blood, or have bloody or black stools.

These are signs of stomach bleeding.

- pain gets worse or lasts more than 10 days
- fever gets worse or lasts more than 3 days
- stomach pain or upset gets worse or lasts
- redness or swelling is present in painful area
- any new symptoms appear

PREGNANCY/BREASTFEEDING

ask a health professional before use. It is especially important not to use ibuprofen during the last 3 months of pregnancy unless definitely directed to do so by a doctor because it may cause a problems in the unborn child or complications during delivery.

KEEP OUT OF REACH OF CHILDREN

In case of overdose, get medical help or contact a PoisonControlCenter right away.

DIRECTIONS

- do not take more than directed
- the smallest effective dose should be used
- do not take longer than 10 days, unless directed by a doctor
  (see Warnings)

adults and children 12 years and older | - take 1 tablet every 4 to 6 hours while symptoms persist - if pain or fever does not respond to 1 tablet, 2 tablets may be used - do not exceed 6 tablets in 24 hours, unless directed by a doctor.
Children under 12 years | - ask a doctor

INACTIVE INGREDIENT(S)

Colloidal silicon dioxide, Croscarmellose Sodium, Magnesium stearate, Microcrystalline sodium, Pregelatinised starch, talc.

STORAGE

- store between 20-25 0c (68-77 0 F).
- do not use if seal under bottle cap imprinted with” SEALED for YOUR PROTECTION” is broken or missing.

PRINCIPAL DISPLAY PANEL

Carton Label PDP
NDC# 68016-295-01
DYE FREE
Ibuprofen Tablets 200 mg
PAIN RELIEVER/FEVER REDUCER (NSAID)
SEE NEW WARNINGS INFORMATION
100 COATED TABLETS
Bottle Label PDP
NDC# 68016-295-01
DYE FREE
Ibuprofen Tablets 200 mg
PAIN RELIEVER/FEVER REDUCER (NSAID)
SEE NEW WARNINGS INFORMATION
100 COATED TABLETS
Carton Label PDP
NDC# 68016-295-50
DYE FREE
Ibuprofen Tablets 200 mg
PAIN RELIEVER/FEVER REDUCER (NSAID)
SEE NEW WARNINGS INFORMATION
50 COATED TABLETS
Bottle Label PDP
NDC# 68016-295-50
DYE FREE
Ibuprofen Tablets 200 mg
PAIN RELIEVER/FEVER REDUCER (NSAID)
SEE NEW WARNINGS INFORMATION
50 COATED TABLETS